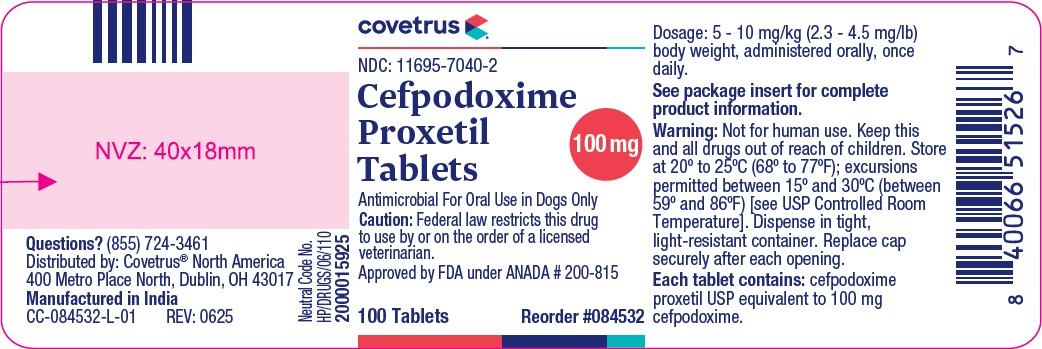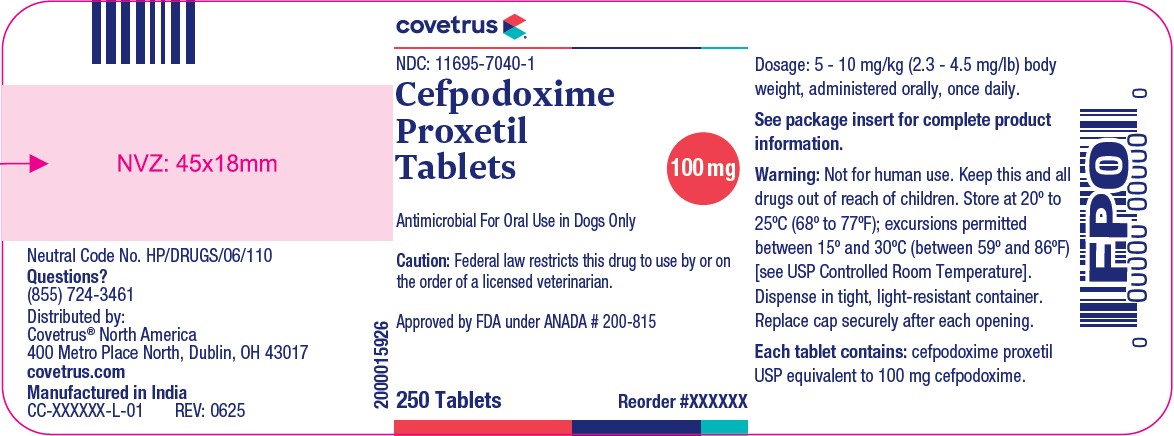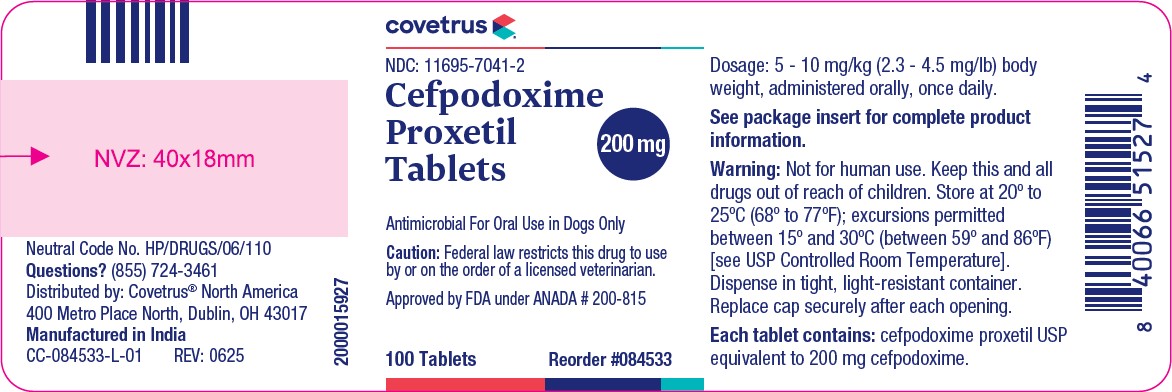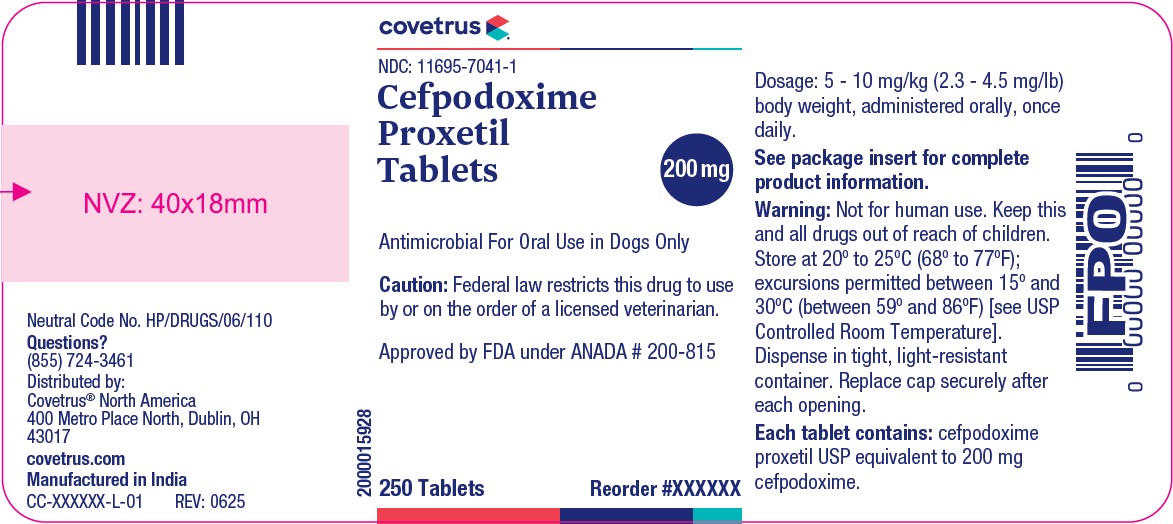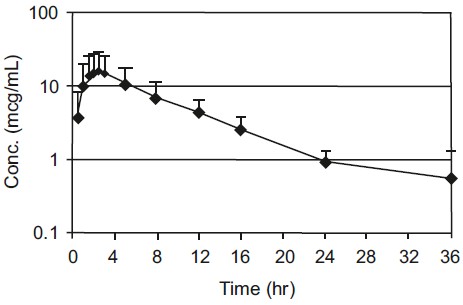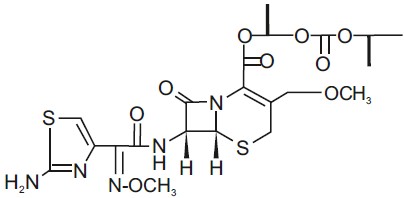 DRUG LABEL: Cefpodoxime Proxetil
NDC: 11695-7040 | Form: TABLET
Manufacturer: BUTLER ANIMAL HEALTH SUPPLY, LLC DBA COVETRUS NORTH AMERICA
Category: animal | Type: Prescription Animal Drug Label
Date: 20250811

ACTIVE INGREDIENTS: CEFPODOXIME PROXETIL 100 mg/1 1

Cefpodoxime Proxetil Tablets
For Oral Use In Dogs Only

CAUTION

Federal law restricts this drug to use by or on the order of a licensed veterinarian.

DESCRIPTION

Cefpodoxime proxetil is an orally administered, extended spectrum, semi-synthetic cephalosporin antibiotic. The chemical name is: (+/-)-1-Hydroxyethyl(+)-(6R,7R)-7-[2-(2-amino-4-thiazolyl) glyoxylamido]-3-methoxymethyl)-8-oxo-5-thia-1-azabicyclo[4.2.0]oct-2-ene-2-carboxylate, 7^2-(Z)- (O-methyloxime), isopropyl carbonate (ester) [87239-81-4].

Cefpodoxime proxetil Chemical Structure:

Cefpodoxime proxetil is a prodrug; its active metabolite is cefpodoxime. All doses of Cefpodoxime Proxetil Tablets are expressed in terms of the active cefpodoxime moiety. Cefpodoxime Proxetil Tablets are available as:

100 mg Tablet, each red-colored, oval-shaped, film-coated, scored tablet contains cefpodoxime proxetil equivalent to 100 mg of cefpodoxime.

200 mg Tablet, each orange-colored, oblong-shaped, film-coated, scored tablet contains cefpodoxime proxetil equivalent to 200 mg of cefpodoxime.

INDICATION

Cefpodoxime Proxetil Tablets are indicated for the treatment of skin infections (wounds and abscesses) in dogs caused by susceptible strains of Staphylococcus pseudintermedius, Staphylococcus aureus, Streptococcus canis (group G, ß hemolytic), Escherichia coli, Pasteurella multocida, and Proteus mirabilis.

DOSAGE AND ADMINISTRATION

Dose range

The dose range of Cefpodoxime Proxetil Tablets is 5-10 mg/kg (2.3-4.5 mg/lb) body weight, administered orally, once a day. The dose may be given with or without food. The determination of dosage for any particular patient must take into consideration such factors as the severity and nature of the infection, the susceptibility of the causative organisms, and the integrity of the patient's host-defense mechanisms. Obtain a sample of the pathogenic organism for culture and sensitivity testing prior to beginning antimicrobial therapy. Once results become available, continue with appropriate therapy.

Duration

Cefpodoxime Proxetil Tablets should be administered once daily for 5-7 days or for 2-3 days beyond the cessation of clinical signs, up to a maximum of 28 days. Treatment of acute infections should not be continued for more than 3-4 days if no response to therapy is seen.

Dosing Charts

For daily oral administration of Cefpodoxime Proxetil Tablets at 5 mg/kg (Table 1) and 10 mg/kg (Table 2).

Table 1. Dose Table for Cefpodoxime Proxetil Tablets at 5 mg/kg Total Daily Dosage

Weight of Dog (lbs)
Daily Dose | 22 | 44 | 66 | 88 | 132
No. of 100 mg tablets | 0.5 | 1 | 1.5 |  | 1
No. of 200 mg tablets |  |  |  | 1 | 1

Weight of Dog (kgs)
Daily Dose | 10 | 20 | 30 | 40 | 60
No. of 100 mg tablets | 0.5 | 1 | 1.5 |  | 1
No. of 200 mg tablets |  |  |  | 1 | 1

Table 2. Dose Table for Cefpodoxime Proxetil Tablets at 10 mg/kg Total Daily Dosage

Weight of Dog (lbs)
Daily Dose | 11 | 22 | 44 | 66 | 88 | 132
No. of 100 mg tablets | 0.5 | 1 |  | 1
No. of 200 mg tablets |  |  | 1 | 1 | 2 | 3

Weight of Dog (kgs)
Daily Dose | 5 | 10 | 20 | 30 | 40 | 60
No. of 100 mg tablets | 0.5 | 1 |  | 1
No. of 200 mg tablets |  |  | 1 | 1 | 2 | 3

CONTRAINDICATIONS

Cefpodoxime proxetil is contraindicated in dogs with known allergy to cefpodoxime or to the ß-lactam (penicillins and cephalosporins) group of antibiotics.

WARNINGS

Not for human use. Keep this and all drugs out of reach of children. Antimicrobial drugs, including penicillins and cephalosporins, can cause allergic reactions in sensitized individuals. To minimize the possibility of allergic reactions, those handling such antimicrobials, including cefpodoxime, are advised to avoid direct contact of the product with the skin and mucous membranes.

PRECAUTIONS

The safety of cefpodoxime proxetil in dogs used for breeding, pregnant dogs, or lactating bitches has not been demonstrated. As with other cephalosporins, cefpodoxime proxetil may occasionally induce a positive direct Coombs' test.

ADVERSE REACTIONS

A total of 216 dogs of various breeds and ages ranging from 2 months to 15 years were included in the field study safety analysis. The following table shows the number of dogs displaying each clinical observation.

Table 3. Abnormal Health Findings in the U.S. Field Study*

Clinical Observation | cefpodoxime proxetil tablets (n=118) | Active Control (n=98)
Vomiting | 2 | 4
Diarrhea | 1 | 1
Increased water drinking | 0 | 2
Decreased appetite | 1 | 1

*Dogs may have experienced more than one of the observations during the study.

CONTACT INFORMATION

To report suspected adverse drug events, for technical assistance or to obtain a copy of the Safety Data Sheet, contact Covetrus® North America at (855) 724-3461 or covetrus.com.

For additional information about adverse drug experience reporting for animal drugs, contact FDA at 1-888- FDA-VETS or http://www.fda.gov/reportanimalae

CLINICAL PHARMACOLOGY

Pharmacokinetics/Pharmacodynamics

Cefpodoxime proxetil is a prodrug that is absorbed from and de-esterified in the gastrointestinal tract to its active metabolite, cefpodoxime. Following oral administration to fasting Beagles, oral bioavailability was 63.1 ± 5.3%.

Figure 1. Canine Plasma Concentration of Cefpodoxime After a Single Oral Dose of 10 mg/kg cefpodoxime proxetil tablets

Cefpodoxime is distributed in the body with an apparent volume of distribution of 151 ± 27 mL/kg. Like other β-lactam antibiotics, cefpodoxime is eliminated from the body primarily in the urine, with an apparent elimination half-life of approximately 5-6 hours after oral administration. This is similar to the 4.7 hour apparent elimination half-life observed after intravenous dosing. Following intravenous administration of 10 mg/kg, the average total body clearance (CIB) was 22.7 ± 4.19 mL/hr/kg.

Table 4. Summary of Pharmacokinetic Parameters Obtained after a Single Oral Dose of 10 mg Cefpodoxime/kg BW, Administered as a Tablet

PK Parameter | Unit | Tablet (SD)
AUC0-∞ | mcg•hr/mL | 145 (77.6)
AUC0-LOQ | mcg•hr/mL | 142 (77.5)
Maximum concentration (Cmax) | mcg/mL | 16.4 (11.8)
Terminal plasma elimination half-life (t1/2,Z) | hr | 5.61 (1.15)
Time of maximum concentration (tmax) | hr | 2.21 (0.542)
Mean residence time (MRT0-∞) | hr | 9.21 (1.97)

Microbiology

Like other β-lactam antibiotics, cefpodoxime exerts its inhibitory effect by interfering with bacterial cell wall synthesis. This interference is primarily due to its covalently binding to the penicillin-binding proteins (PBPs) (i.e. transpeptidase and/or carboxypeptidase), which are essential for synthesis of the bacterial cell wall. Therefore, cefpodoxime is bactericidal. Cefpodoxime is stable in the presence of many common β-lactamase enzymes. As a result, many organisms resistant to other β-lactam antibiotics (penicillins and some cephalosporins) due to the production of β-lactamases may be susceptible to cefpodoxime.

Cefpodoxime has a broad spectrum of clinically useful antibacterial activity that includes staphylococci, streptococci, and Gram-negative species (including Pasteurella, Escherichia, and Proteus). The compound is not active against most obligate anaerobes, Pseudomonas spp., or enterococci. The minimum inhibitory concentrations (MICs) for cefpodoxime against Gram-positive and Gram-negative pathogens isolated from canine skin infections (wounds and abscesses) in a 2002 U.S. field study are presented in Table 5. All MICs were determined in accordance with the National Committee for Clinical Laboratory Standards (NCCLS). Appropriate quality control (QC) ranges for in vitro susceptibility testing are presented in Table 6.

Table 5. Cefpodoxime Minimum Inhibitory Concentration Values (mcg/mL) from a 2002 Field Study Evaluating Skin Infections (wounds and abscesses) of Canines in the United States.

Organism* | # of Isolates | MIC50 | MIC90 | Range
Staphylococcus pseudintermedius | 118 | 0.12 | 0.50 | 0.12->32.0
Streptococcus canis (group G, β hemolytic) | 33 | ≤0.03 | ≤0.03 | ≤0.03†
Escherichia coli | 41 | 0.25 | 0.50 | 0.12->32.0
Pasteurella multocida | 32 | ≤0.03 | ≤0.03 | ≤0.03-0.12
Proteus mirabilis | 14 | ≤0.03 | 0.06 | ≤0.03-0.06
Staphylococcus aureus | 19 | 2.0 | 2.0 | 0.12-2.0

* Veterinary specific interpretive criteria have not been established for the above listed canine pathogens by the NCCLS at this time.

† No Range, all isolates yielded the same value.

Table 6. Acceptable Quality Control Ranges for Cefpodoxime

QC ATCC strain | KB Disk Diffusion Method |  | Broth Micro-dilution Method
QC ATCC strain | Drug concentration | Zone diameter | MIC
Escherichia coli 25922 | 10 mcg | 23-28 mm* | 0.25-1 mcg/mL*
Staphylococcus aureus 25923 | 10 mcg | 19-25 mm*
Staphylococcus aureus 29213 |  |  | 1-8 mcg/mL*
Streptococcus pneumoniae 49619 | 10 mcg | 28-34 mm† | 0.03-0.12 mcg/mL†

*These ranges are for quality control strains used to monitor accuracy of minimum inhibitory concentrations (MICs) of non-fastidious organisms using cation-adjusted Mueller-Hinton agar or broth medium. The dilution range should encompass the QC ranges of these strains in the broth micro-dilution method.

†These ranges are for quality control strains used to monitor accuracy of minimum inhibitory concentrations (MICs) of fastidious organisms. When susceptibility testing is performed for Streptococcus canis (group G, β hemolytic), Streptococcus pneumoniae ATCC 49619 should be included as a QC strain in the presence of 5% lysed sheep blood (KB disk diffusion method) or 2.5% lysed horse blood (broth micro-dilution method).

EFFECTIVENESS

The clinical effectiveness of cefpodoxime proxetil tablets was established in a multi-location (23 site) field study. In this study, 216 dogs with infected wounds or abscesses were treated with either cefpodoxime proxetil tablets (n=118) once daily at 5 mg/kg (2.3 mg/lb) body weight or with an active control antibiotic (n=98) administered twice daily for 5-7 days. In this study, cefpodoxime proxetil tablets were considered noninferior to the active control (88.7% versus 88.4% respectively) in the treatment of canine skin infections (wounds and abscesses) caused by susceptible strains of Staphylococcus pseudintermedius, Staphylococcus aureus, Streptococcus canis (group G, β hemolytic), Escherichia coli, Pasteurella multocida, and Proteus mirabilis.

ANIMAL SAFETY

In target animal safety studies, cefpodoxime was well tolerated at exaggerated daily oral doses of 100 mg/kg/day (10 times the maximum label dose) for 13 weeks in adult dogs and for 28 days in puppies (18-23 days of age). Therefore, once daily administration of cefpodoxime oral tablets at the maximum labeled dose of 10 mg/kg for up to 28 days was shown to be safe in adult dogs and puppies.

Blood dyscrasia including neutropenias, may be seen following high doses of cephalosporins. Cephalosporin administration should be discontinued in such cases.

STORAGE INFORMATION

Store at 20° to 25°C (68° to 77°F); excursions permitted between 15° and 30°C (between 59° and 86°F) [see USP Controlled Room Temperature]. Dispense in tight, light-resistant container. Replace cap securely after each opening.

HOW SUPPLIED

Cefpodoxime Proxetil Tablets are available in the following strengths (cefpodoxime equivalent), colors, and sizes:

100 mg (Red-colored, oval-shaped, film-coated tablet, debossed with "F" & "3" on either side of score line on one side of tablets and "1" & "00" on either side of score line on other side of the tablet.)

Bottles of 100 | NDC 11695-7040-2
Bottles of 250 | NDC 11695-7040-1

200 mg (Orange-colored, oblong-shaped, film-coated tablet, debossed with "F" & "3" on either side of score line on one side of tablets and "2" & "00" on either side of score line on other side of the tablet.)

Bottles of 100 | NDC 11695-7041-2
Bottles of 250 | NDC 11695-7041-1

Approved by FDA under ANADA # 200-815

Questions?
(855) 724-3461

Distributed by:
Covetrus® North America
400 Metro Place North
Dublin, OH 43017
covetrus.com

Manufactured in India
Neutral Code No. HP/DRUGS/06/110
CC-CefpodoximeTabPI-01
REV: 0625
© 2025 Covetrus, Inc. All rights reserved.

PACKAGE LABEL.PRINCIPAL DISPLAY PANEL

NDC: 11695-7040-2

Cefpodoxime Proxetil Tablets

100 mg

Antimicrobial For Oral Use in Dogs Only

Caution: Federal law restricts this drug to use by or on the order of a licensed veterinarian.

Approved by FDA under ANADA # 200-815

100 Tablets

PACKAGE LABEL.PRINCIPAL DISPLAY PANEL

NDC: 11695-7040-1

Cefpodoxime Proxetil Tablets

100 mg

Antimicrobial For Oral Use in Dogs Only

Caution: Federal law restricts this drug to use by or on the order of a licensed veterinarian.

Approved by FDA under ANADA # 200-815

250 Tablets

PACKAGE LABEL.PRINCIPAL DISPLAY PANEL

NDC: 11695-7041-2

Cefpodoxime Proxetil Tablets

200 mg

Antimicrobial For Oral Use in Dogs Only

Caution: Federal law restricts this drug to use by or on the order of a licensed veterinarian.

Approved by FDA under ANADA # 200-815

100 Tablets

PACKAGE LABEL.PRINCIPAL DISPLAY PANEL

NDC: 11695-7041-1

Cefpodoxime Proxetil Tablets

200 mg

Antimicrobial For Oral Use in Dogs Only

Caution: Federal law restricts this drug to use by or on the order of a licensed veterinarian.

Approved by FDA under ANADA # 200-815

250 Tablets